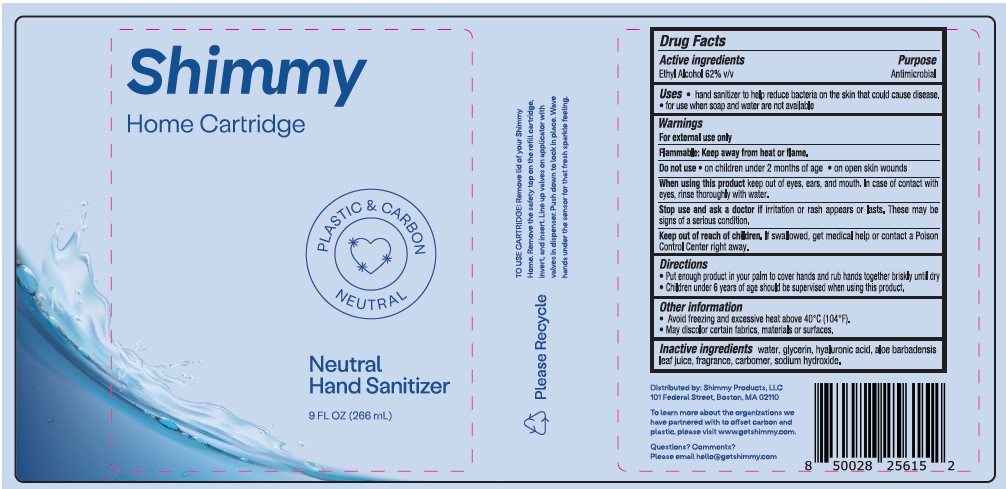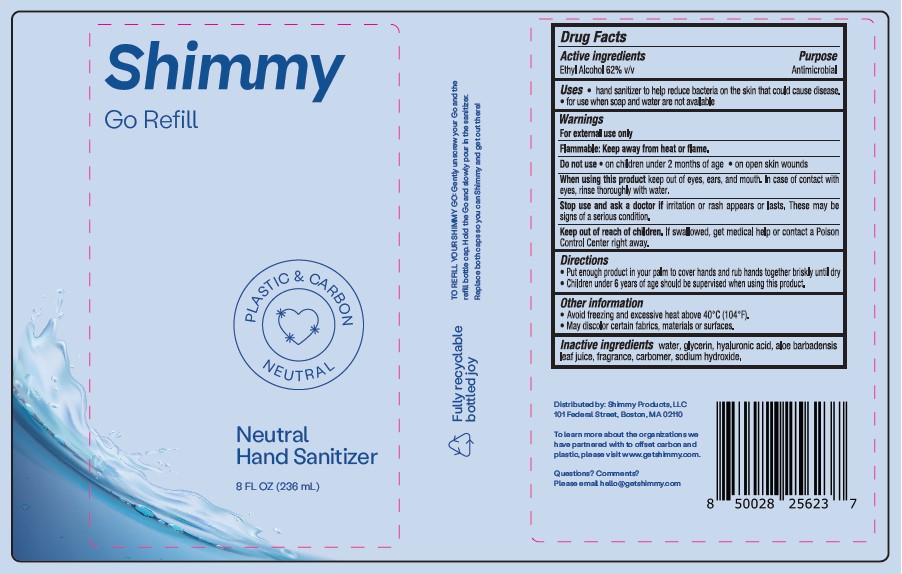 DRUG LABEL: Shimmy Neutral Hand Sanitizer
NDC: 81755-004 | Form: SPRAY
Manufacturer: Shimmy Products LLC
Category: otc | Type: HUMAN OTC DRUG LABEL
Date: 20240725

ACTIVE INGREDIENTS: ALCOHOL 62 mg/100 mL
INACTIVE INGREDIENTS: HYALURONATE SODIUM; SODIUM HYDROXIDE; GLYCERIN; ALOE VERA LEAF; WATER; CARBOMER HOMOPOLYMER TYPE C

SHIMMY NEUTRAL HAND SANITIZER

Active Ingredients

Ethyl Alcohol 62% v/v

Purpose

Antimicrobial

Uses

- hand sanitizer to help reduce bacteria on the skin that could cause disease.
- for use when soap and water are not available

Warnings

For external use only.

Flammable. Keep away from heat or flame.

Do not use

- on children less than 2 months of age
- on open skin wounds

When using this product

- keep out of eyes, ears, and mouth. In case of contact with eyes, rinse eyes thoroughly with water.

Stop use and ask a doctor

if irritation or rash appears or lasts. These may be signs of a serious condition.

Keep out of reach of children.

If swallowed, get medical help or contact a Poison Control Center right away.

Directions

- Put enough product in your palm to cover your hands and rub hands together briskly until dry
- Children under 6 years of age should be supervised when using this product.

Other information

- Avoid freezing and excessive heat above 40ºC (104ºF).
- May discolor certain fabrics, materials or surfaces.

Inactive ingredients

water, glycerin, hyaluronic acid, aloe barbadensis leaf juice, fragrance, carbomer, sodium hydroxide.